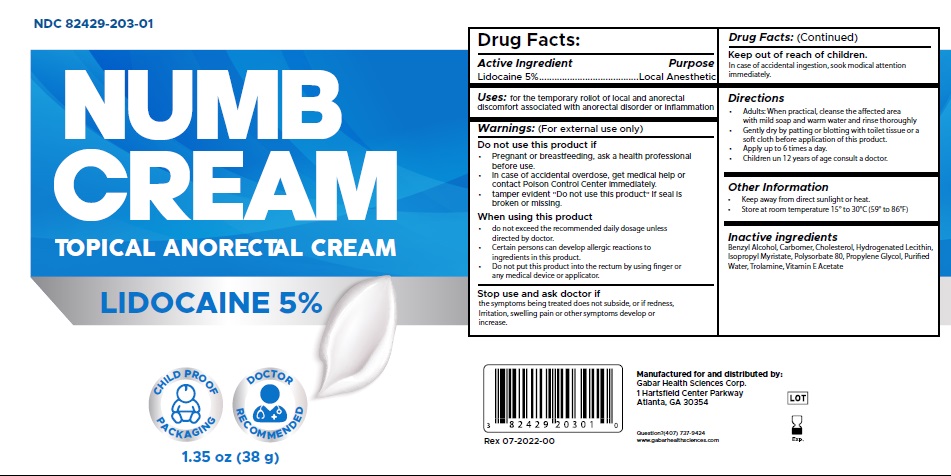 DRUG LABEL: NUMB
NDC: 82429-203 | Form: CREAM
Manufacturer: Gabar Health Sciences Corp.
Category: otc | Type: HUMAN OTC DRUG LABEL
Date: 20231021

ACTIVE INGREDIENTS: LIDOCAINE 50 mg/1 g
INACTIVE INGREDIENTS: PROPYLENE GLYCOL; HYDROGENATED SOYBEAN LECITHIN; TROLAMINE; ISOPROPYL MYRISTATE; BENZYL ALCOHOL; CARBOMER HOMOPOLYMER, UNSPECIFIED TYPE; POLYSORBATE 80; .ALPHA.-TOCOPHEROL ACETATE; CHOLESTEROL; WATER

NUMB CREAM

Active Ingredient

Lidocaine 5% W/W

Purpose

Local Anesthetic

Uses

For the temporary roliot of local and anorectal discomfort associated with anorectal disorder or inflammation.

Warnings (For external use only)

Do not use this product if

- Pregnant or breastfeeding, ask a health professional before use.
- In case of accidental overdose, get medical help or contact Poison Control Center immediately.
- tamper evident "Do not use this product" If seal is broken or missing.

When using this product

- do not exceed the recommended daily dosage unless directed by doctor.
- Certain persons can develop allergic reactions to ingredients in this product.
- Do not put this product into the rectum by using ‑nger or any medical device or applicator.

Stop use and ask doctor if

the symptoms being treated does not subside, or if redness, Irritation, swelling pain or other symptoms develop or increase.

Keep out of reach of the children.

In case of accidental ingestion, sook modical attention immediately.

Directions

- Adults: When practical, cleanse the affected area with mild soap and warm water and rinse thoroughly
- Gently dry by patting or blotting with toilet tissue or a soft cloth before application of this product.
- Apply up to 6 times a day.
- Children un 12 years of age consult a doctor.

Other Information

• Keep away from direct sunlight or heat.

• Store at room temperature 15° to 30°C (59° to 86°F)

Inactive ingredient

Benzyl Alcohol, Carbomer, Cholesterol, Hydrogenated Lecithin, Isopropyl Myristate, Polysorbate 80, Propylene Glycol, Purfied Water, Trolamine, Vitamin E Acetate

Questions ?

(407) 737-9424

Principal Primary Panel

NUMB CREAM

NDC 82429-203-01

Lidocaine Cream 5%

NET WT 1.35 OZ (38g)